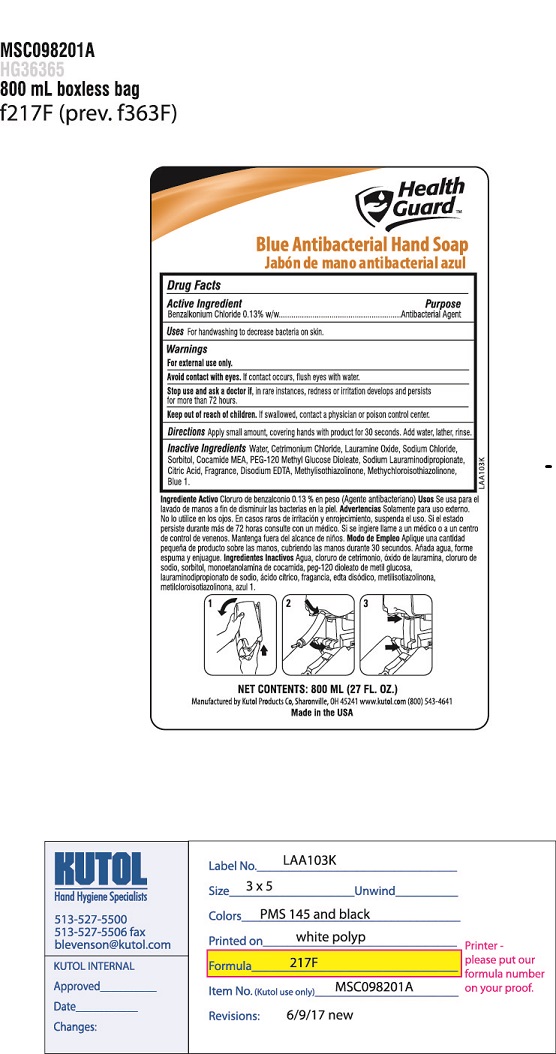 DRUG LABEL: Health Guard Antibacterial Hand cleanser
NDC: 50865-217 | Form: SOAP
Manufacturer: Kutol Products Company
Category: otc | Type: HUMAN OTC DRUG LABEL
Date: 20190116

ACTIVE INGREDIENTS: BENZALKONIUM CHLORIDE 0.013 mg/1 mL
INACTIVE INGREDIENTS: WATER; SODIUM CHLORIDE; CETRIMONIUM CHLORIDE; LAURAMINE OXIDE; SORBITOL; COCO MONOETHANOLAMIDE; FD&C BLUE NO. 1; PEG-120 METHYL GLUCOSE DIOLEATE; METHYLISOTHIAZOLINONE; METHYLCHLOROISOTHIAZOLINONE; EDETATE DISODIUM ANHYDROUS; CITRIC ACID MONOHYDRATE

Active Ingredient

Benzalkonium Chloride 0.13% w/w

Ingrediente activo
Cloruro de benzalconio

Purpose

Antibacterial agent

Propósito
Agente antibacteriano

Keep out of reach of children. If swallowed, a physician or contact a poison control center right away.

Manténgase fuera del alcance de los niños. Si se ingiere, consulte a un médico o contacte inmediatamente con un centro de control de envenenamiento.

INDICATIONS AND USAGE

Uses For handwashing to decrease bacteria on the skin.

Usos Para lavar las manos para disminuir las bacterias en la piel.

Directions

- Apply a small amount, covering hands with product for 30 seconds. Add water, lather and rinse.

Direcciones
Aplique una pequeña cantidad, cubriendo las manos con el producto durante 30 segundos. Añada agua, espolvoree y enjuague

Inactive Ingredients

water, cetrimonium chloride, lauramine oxide, sorbitol, cocamide MEA, sodium chloride, PEG-120 methyl glucose dioleate, sodium lauraminodipropionate, citric acid, fragrance, disodium EDTA, methyisothiazolinone, methylchloroisothiazolinone, blue 1.

Ingredientes inactivos
agua, cloruro de cetrimonio, óxido de lauramina, sorbitol, cocamida MEA, cloruro de sodio, PEG-120 metil diolato de glucosa, lauraminodipropionato de sodio, ácido cítrico, fragancia, EDTA disódico, metiisotiazolinona, metilcloroisotiazolinona, azul 1.

Warnings
For external use only.
Avoid contact with eyes. If contact occurs, flush with water.
Stop use and ask a doctor if in rare instances, redness and irritation develops and persists.

Advertencias
Sólo para uso externo.
Evitar el contacto con los ojos.
Deje de usar y consulte a un médico si en raras ocasiones se desarrolla y persiste enrojecimiento e irritación.